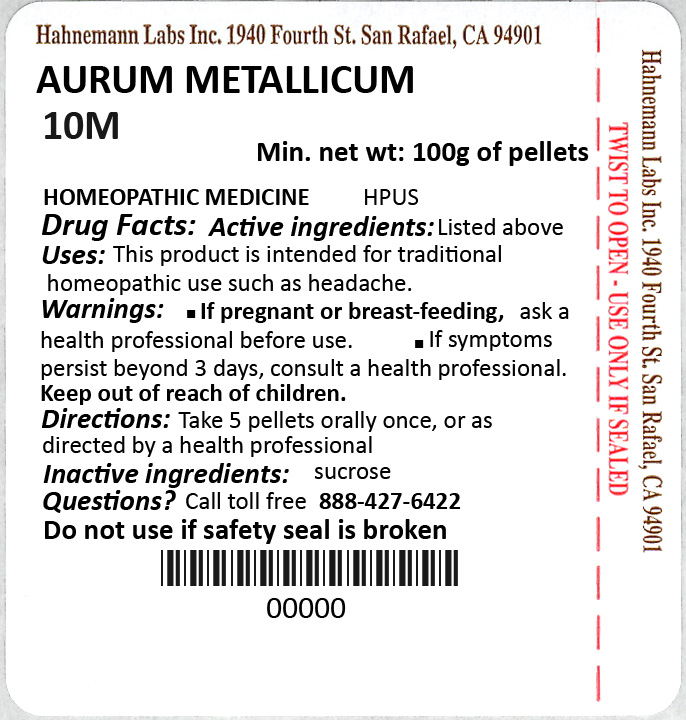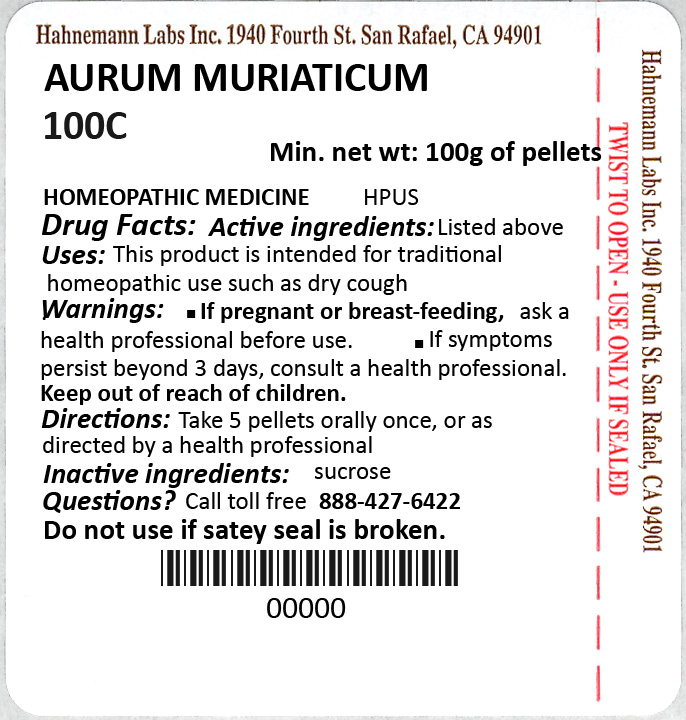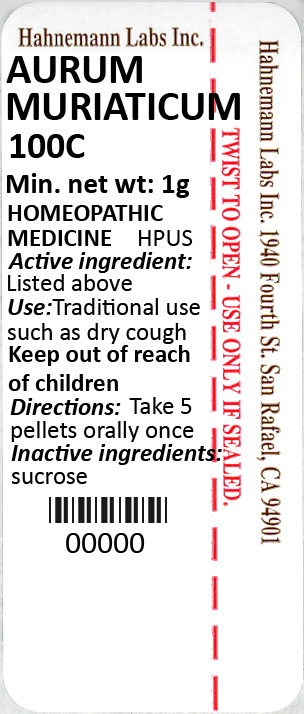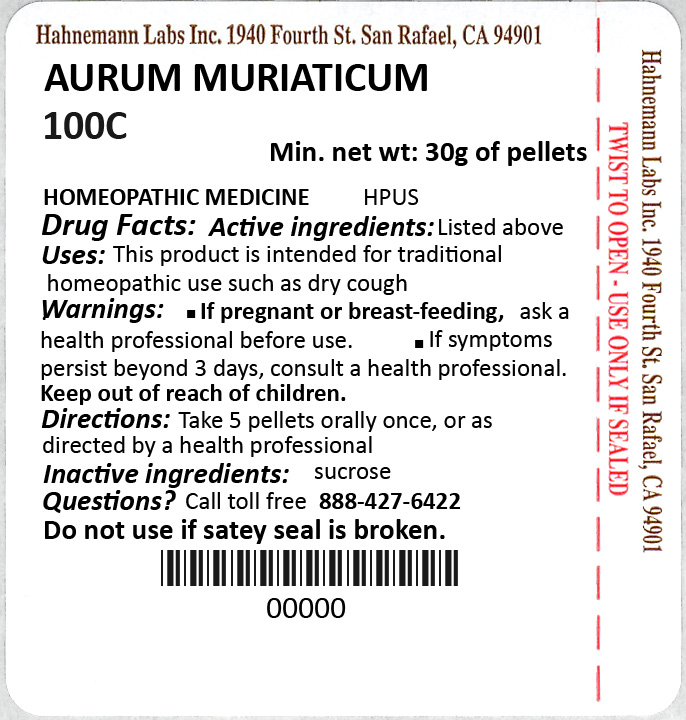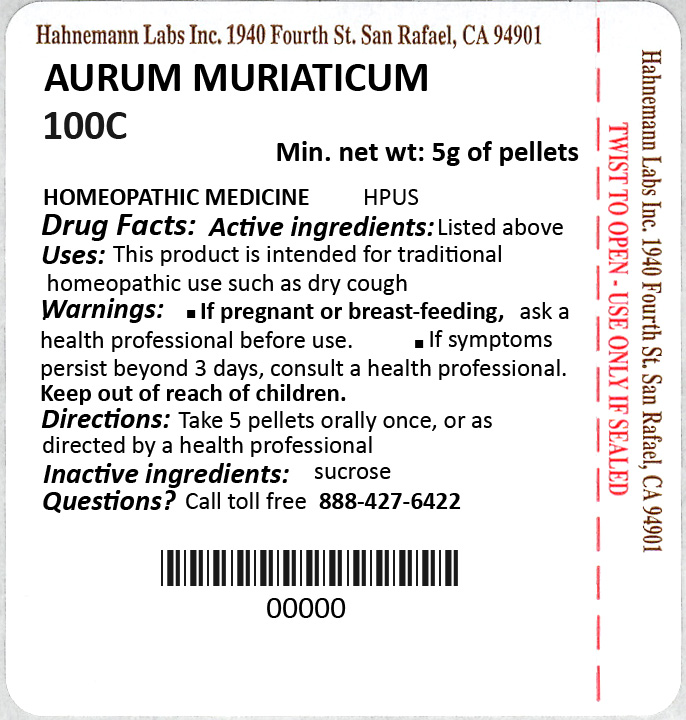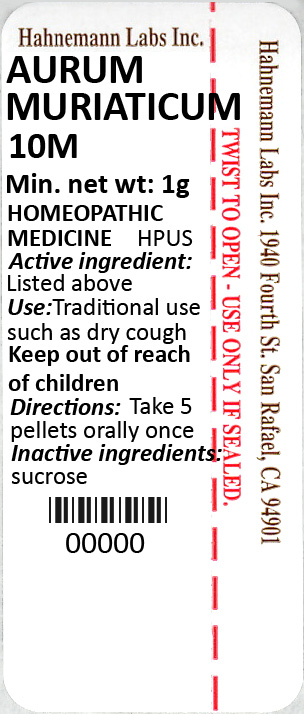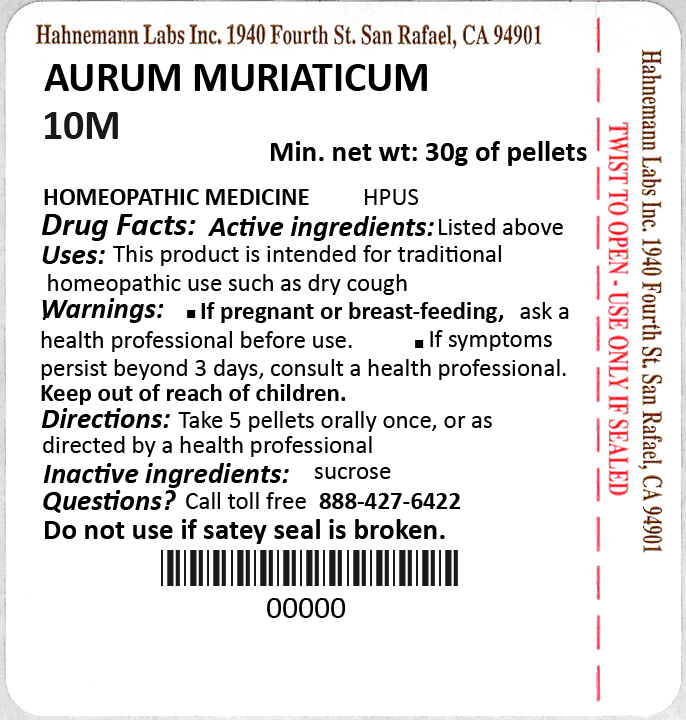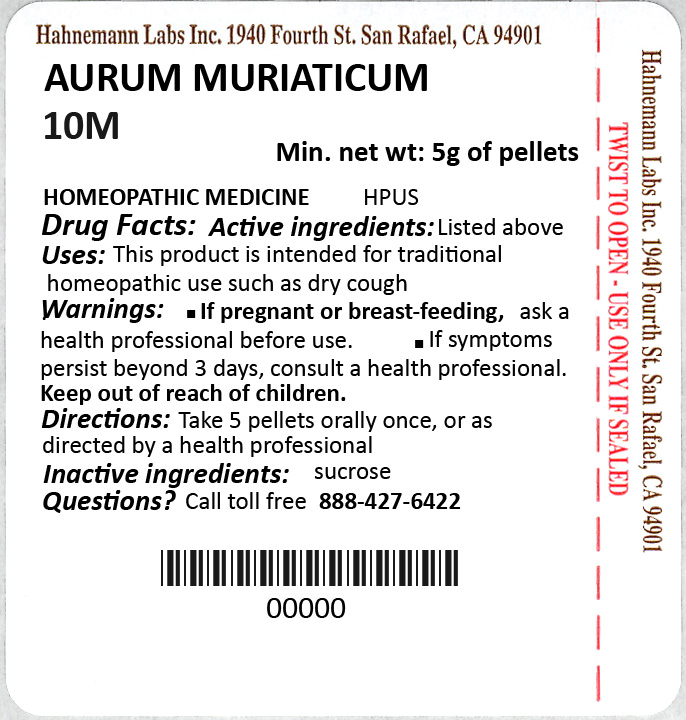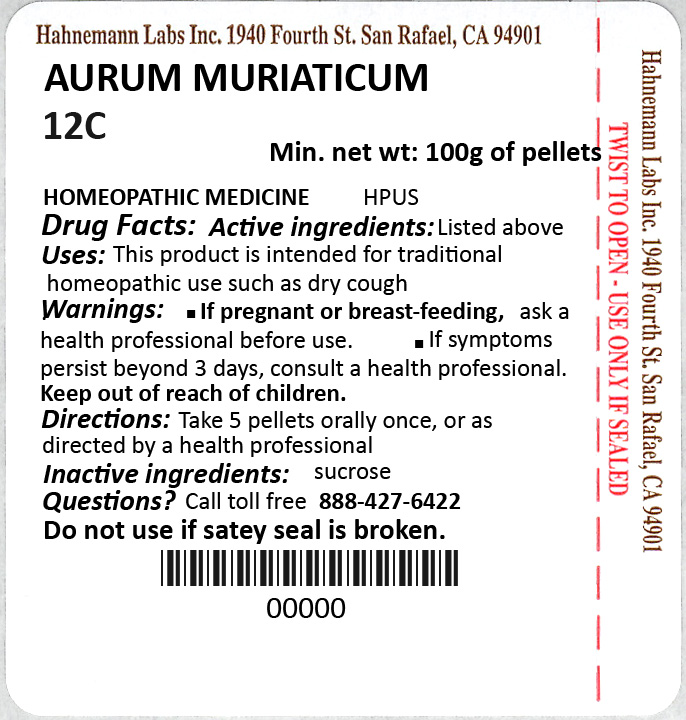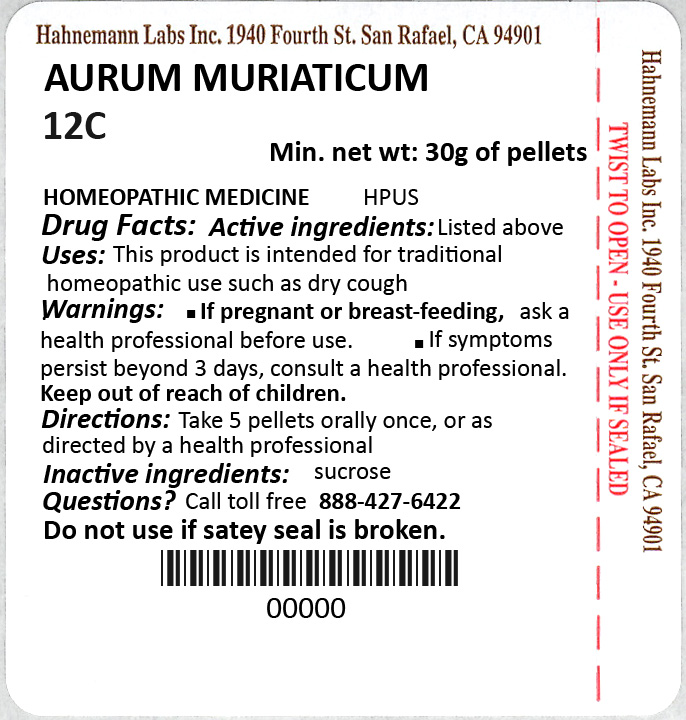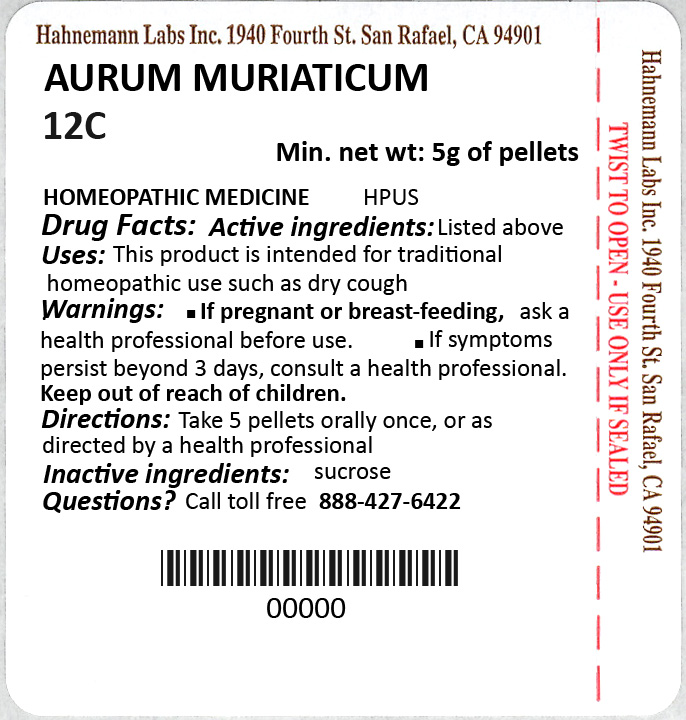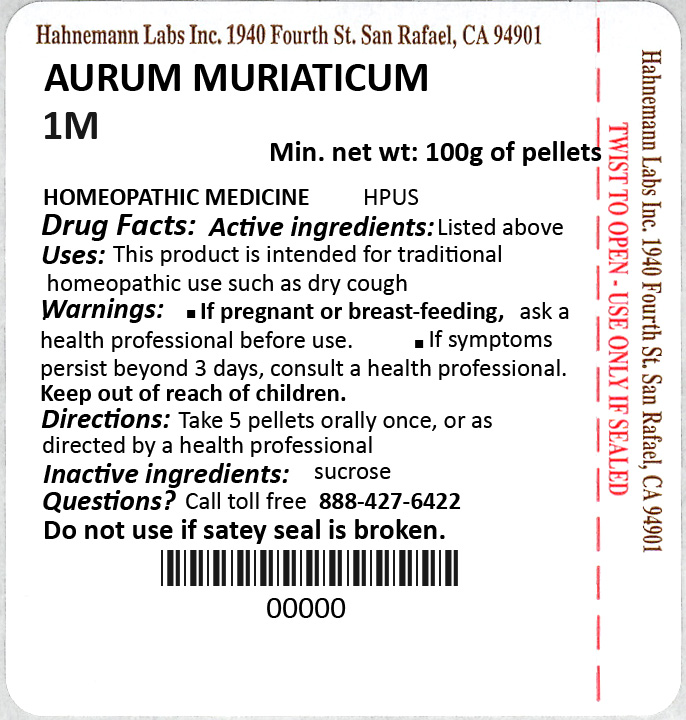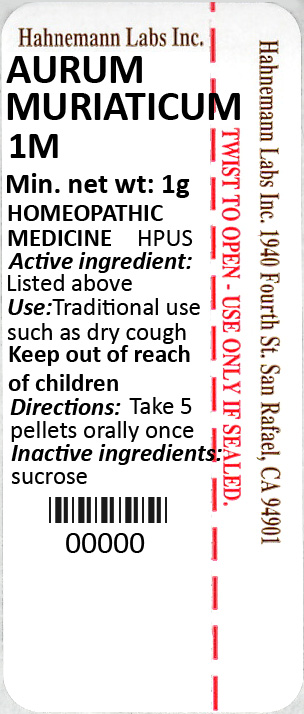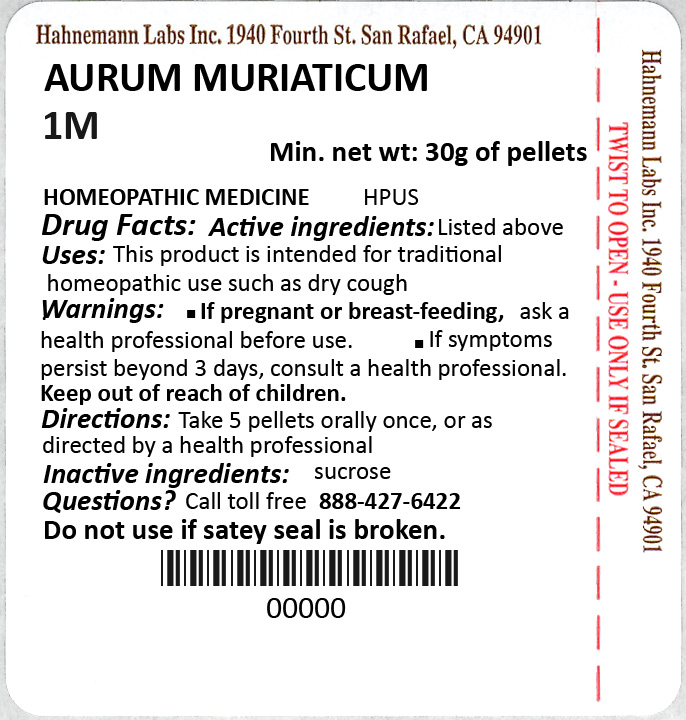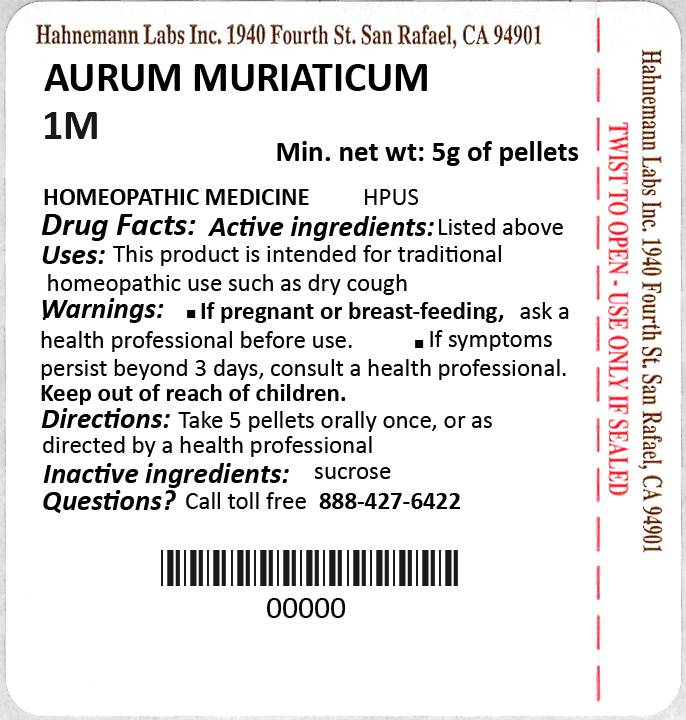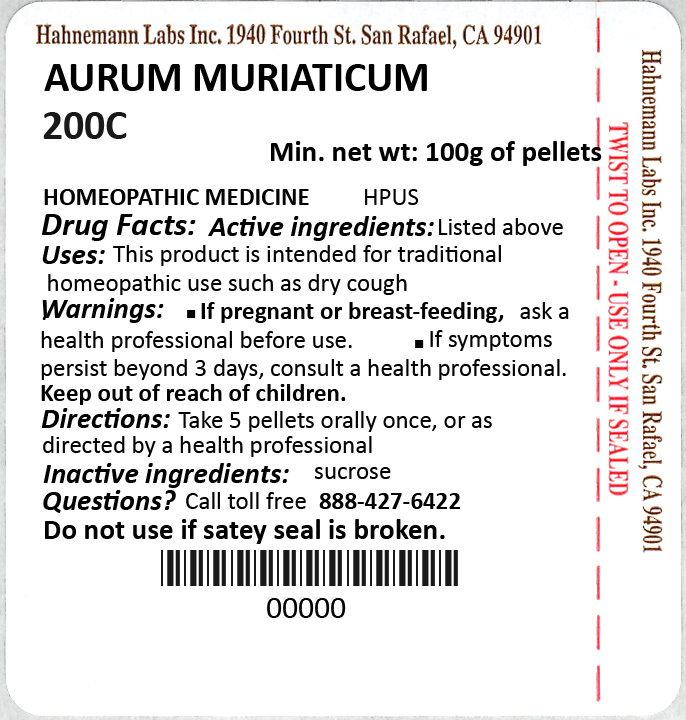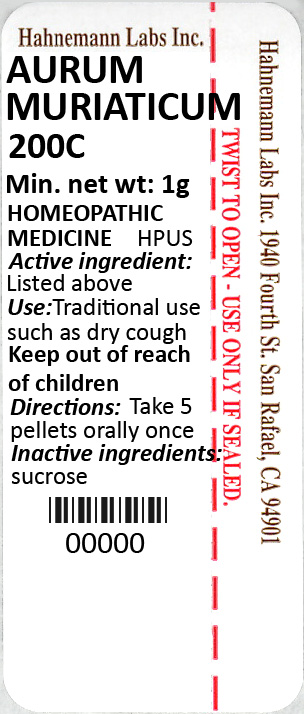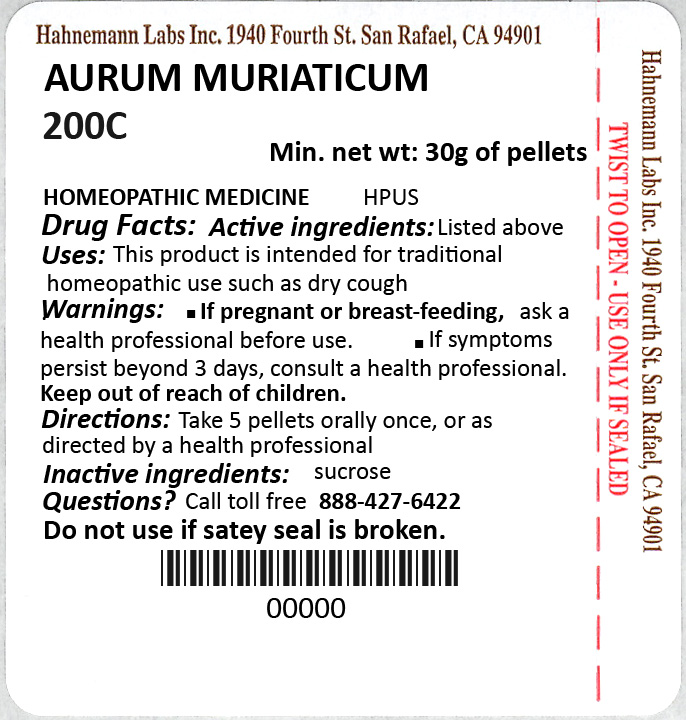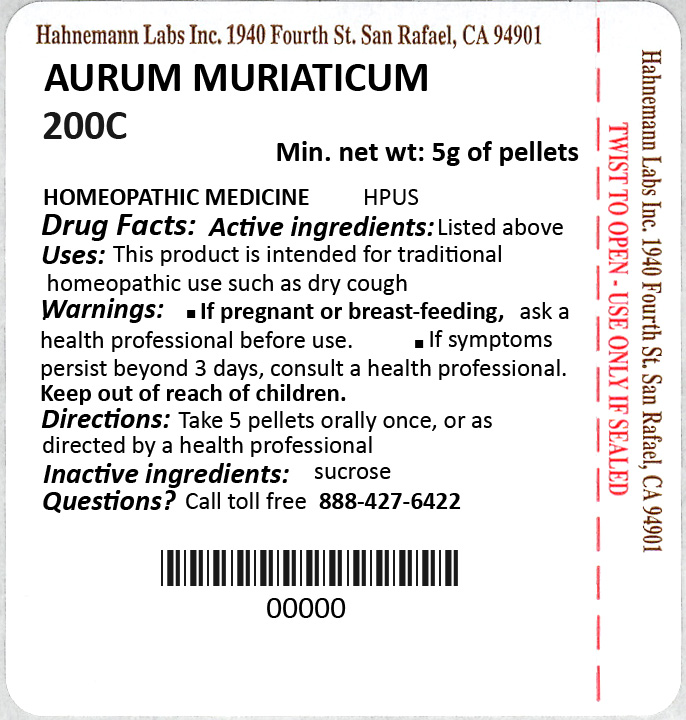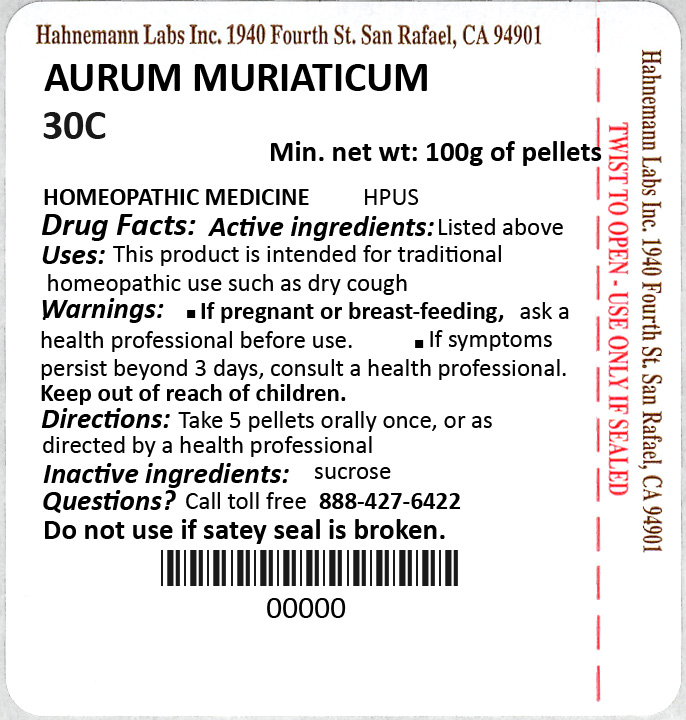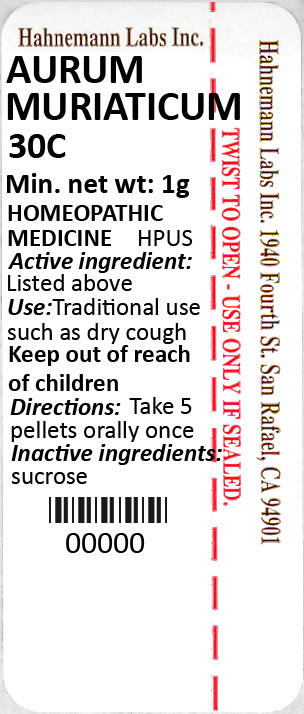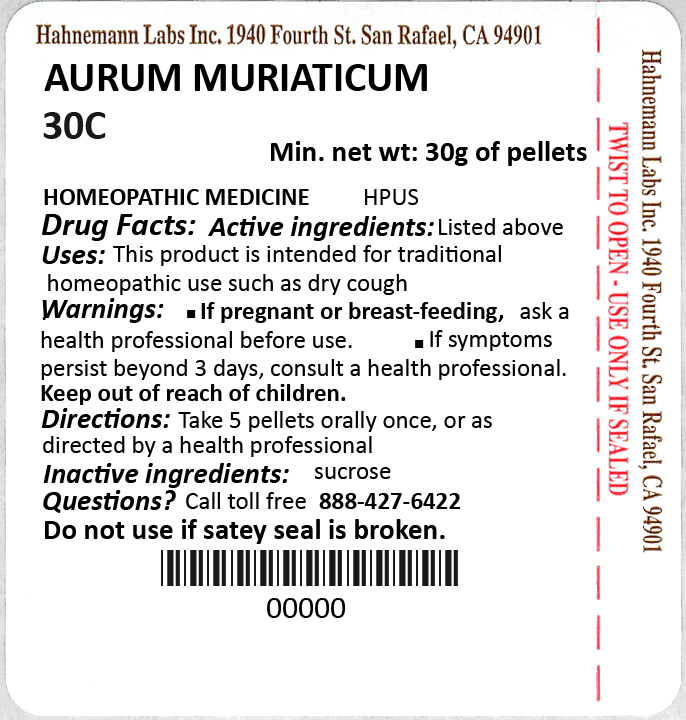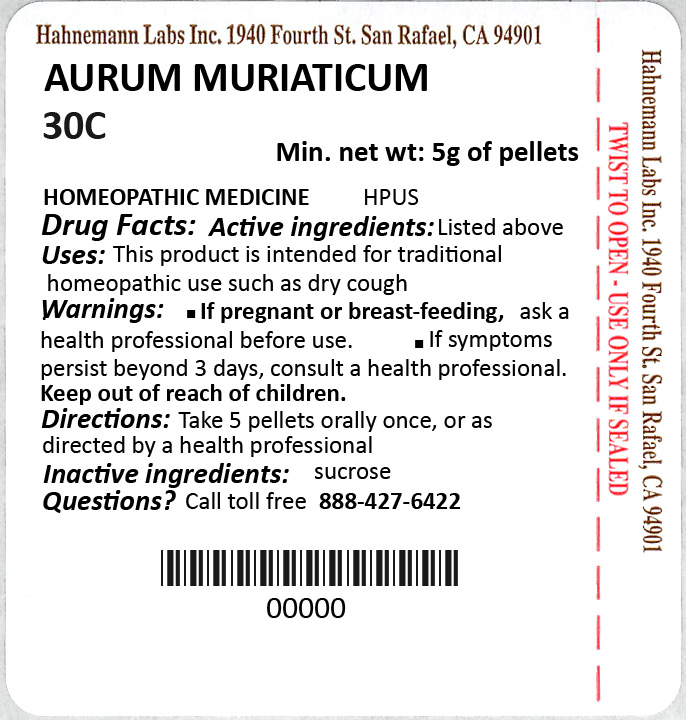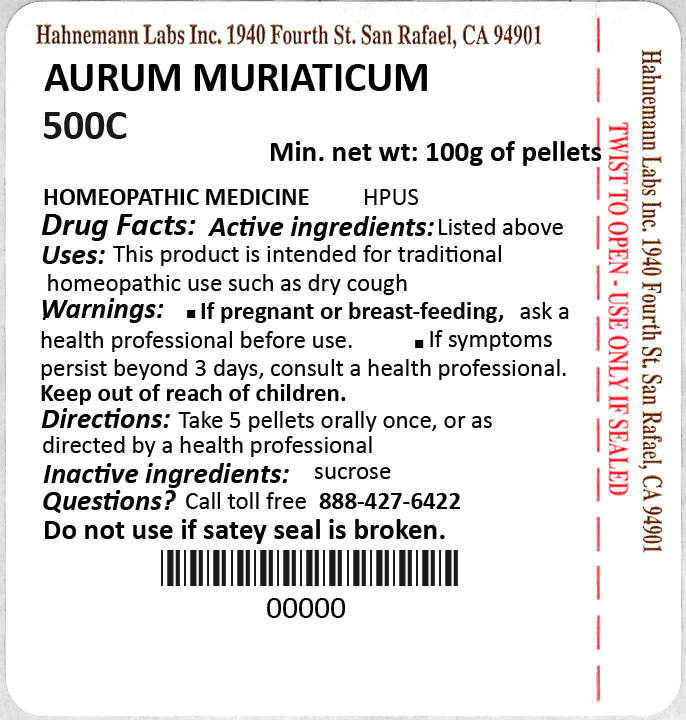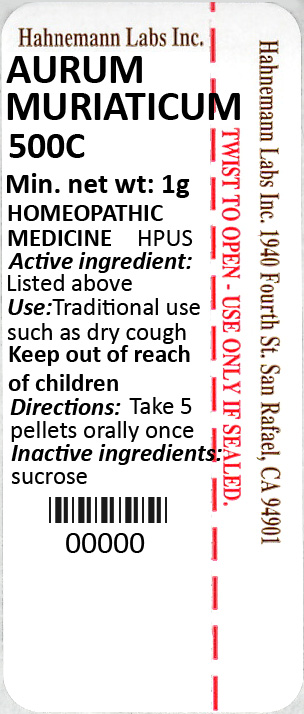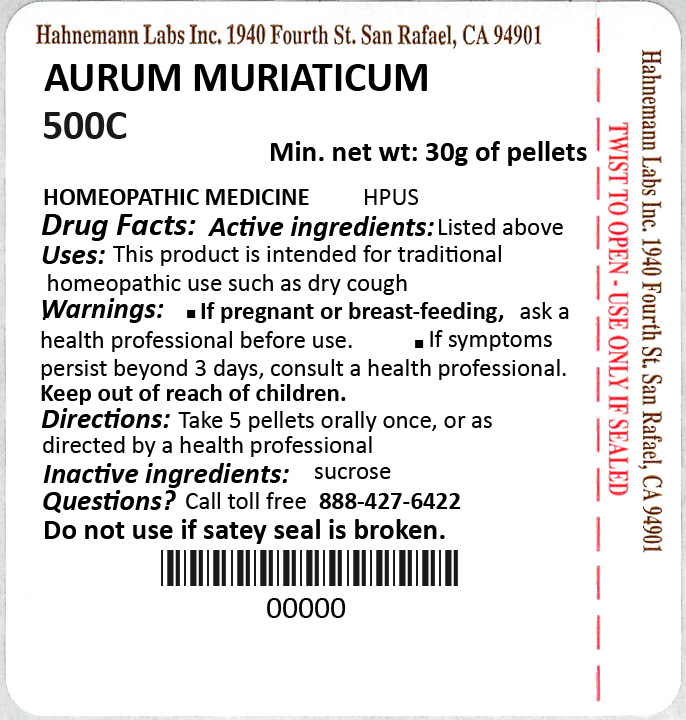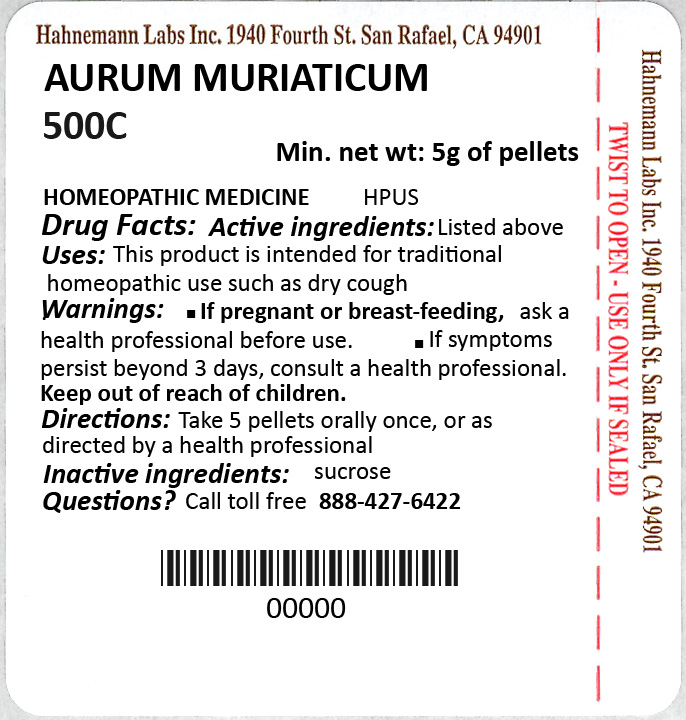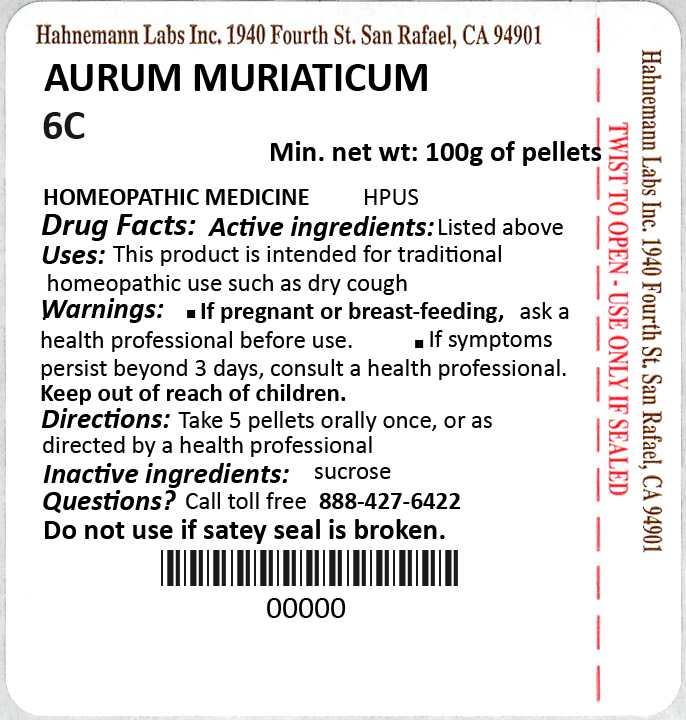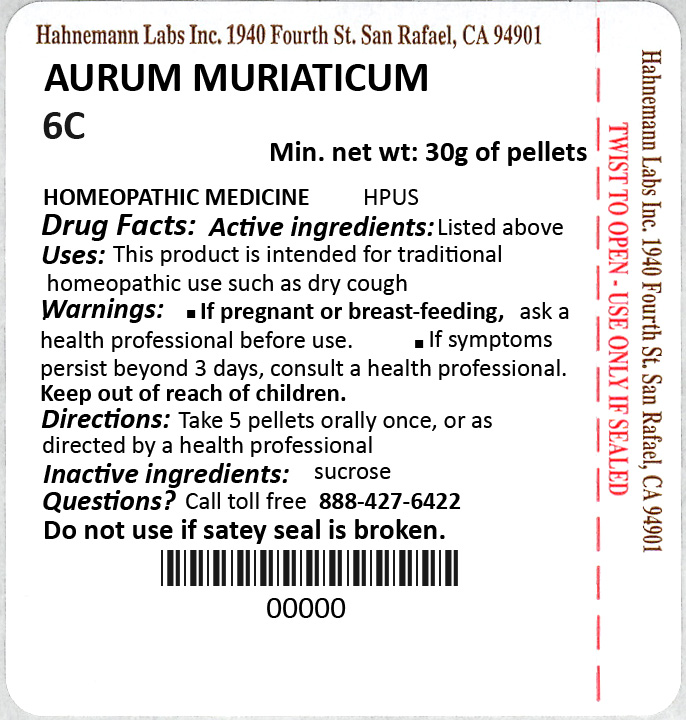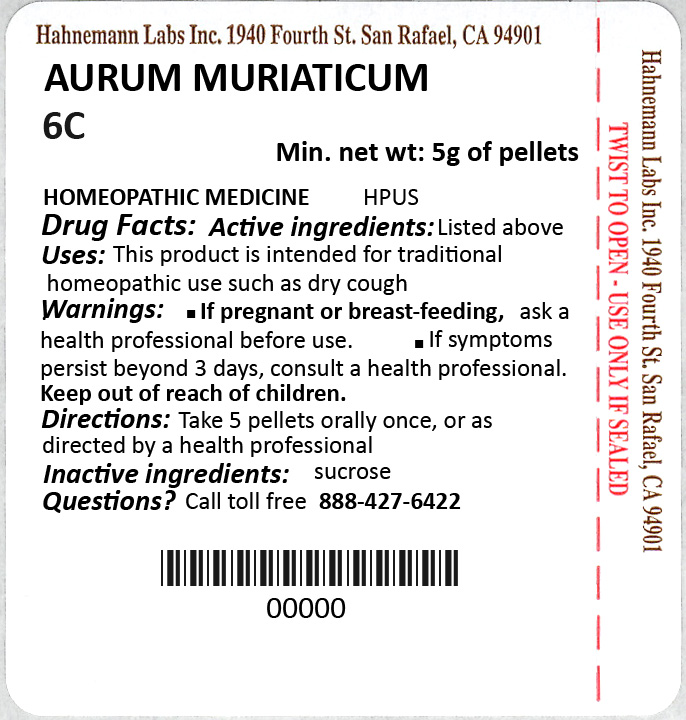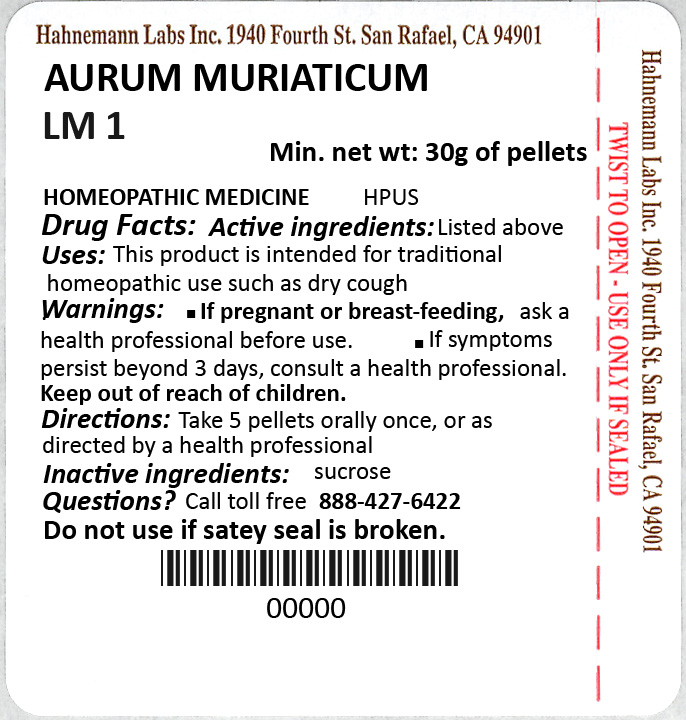 DRUG LABEL: Aurum Muriaticum
NDC: 63545-310 | Form: PELLET
Manufacturer: Hahnemann Laboratories, Inc.
Category: homeopathic | Type: HUMAN OTC DRUG LABEL
Date: 20210415

ACTIVE INGREDIENTS: GOLD TRICHLORIDE 30 [hp_C]/1 1
INACTIVE INGREDIENTS: SUCROSE

PACKAGE LABEL

l